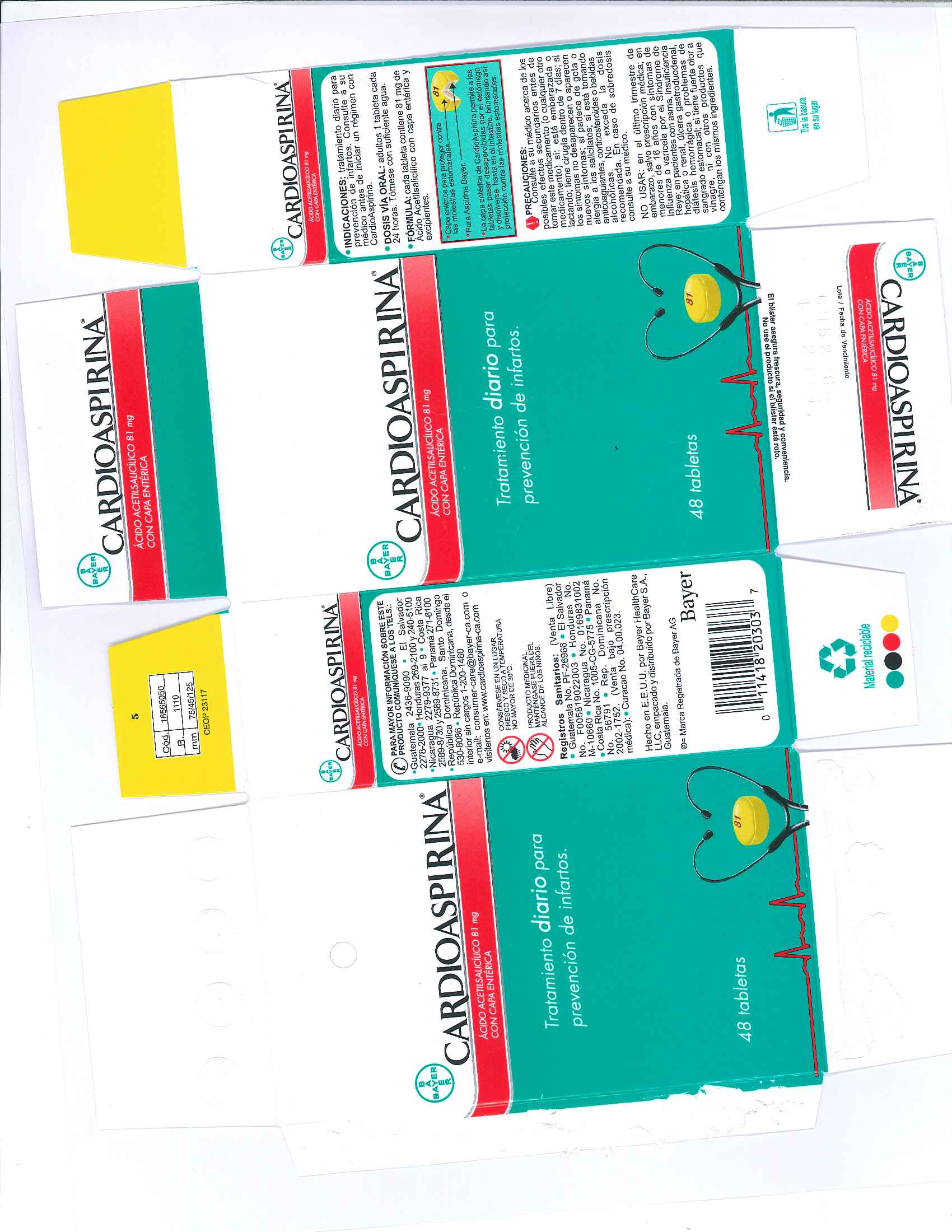 DRUG LABEL: Cardiospirina 81 mg Tabletas con cubierta enterica
NDC: 0280-2065 | Form: TABLET
Manufacturer: Bayer HealthCare LLC.
Category: otc | Type: HUMAN OTC DRUG LABEL
Date: 20250117

ACTIVE INGREDIENTS: ASPIRIN 81 mg/1 1
INACTIVE INGREDIENTS: METHACRYLIC ACID - ETHYL ACRYLATE COPOLYMER (1:1) TYPE A; POWDERED CELLULOSE; SHELLAC; SODIUM LAURYL SULFATE; CARNAUBA WAX; D&C YELLOW NO. 10; ALUMINUM OXIDE; POLYSORBATE 80; PROPYLENE GLYCOL; TRIACETIN; TRIETHYL CITRATE; FERROSOFERRIC PHOSPHATE; FD&C YELLOW NO. 6; BROWN IRON OXIDE; HYPROMELLOSES; STARCH, CORN

Cardioaspirina 81 mg Tablets con cubierta enterica